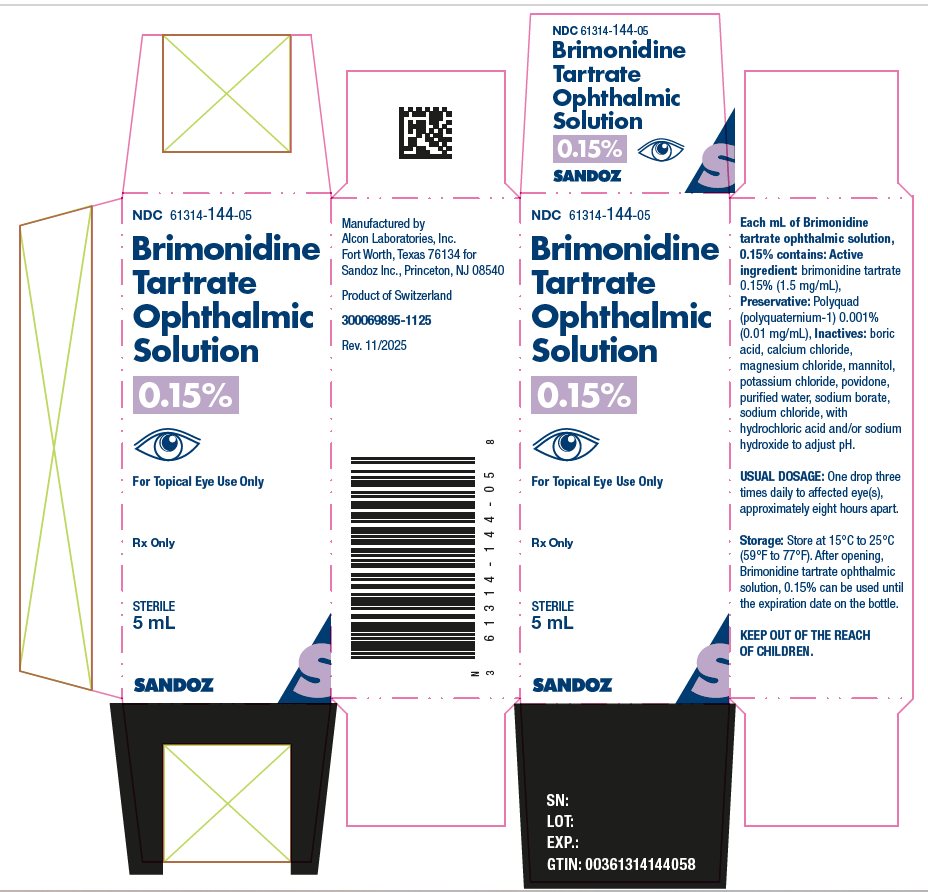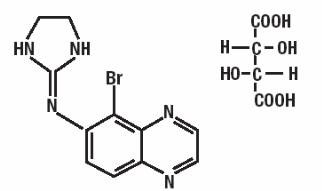 DRUG LABEL: Brimonidine Tartrate
NDC: 61314-144 | Form: SOLUTION
Manufacturer: Sandoz Inc
Category: prescription | Type: HUMAN PRESCRIPTION DRUG LABEL
Date: 20251124

ACTIVE INGREDIENTS: BRIMONIDINE TARTRATE 1.5 mg/1 mL
INACTIVE INGREDIENTS: POVIDONE, UNSPECIFIED; BORIC ACID; SODIUM BORATE; CALCIUM CHLORIDE; POTASSIUM CHLORIDE; MANNITOL; SODIUM CHLORIDE; WATER; HYDROCHLORIC ACID; SODIUM HYDROXIDE

HIGHLIGHTS OF PRESCRIBING INFORMATION

These highlights do not include all the information needed to use BRIMONIDINE TARTRATE OPHTHALMIC SOLUTION safely and effectively. See full prescribing information for BRIMONIDINE TARTRATE OPHTHALMIC SOLUTION.
BRIMONIDINE TARTRATE OPHTHALMIC SOLUTION, 0.15%, for topical ophthalmic use
Initial U.S. Approval: 1996

RECENT MAJOR CHANGES

- Contraindications, Neonates and Infants (Pediatric Patients Younger than 2 Years Old) (4.1) 11/2025
- Warnings and Precautions, Severe Cardiovascular Disease (5.2) 11/2025
- Warnings and Precautions, Contamination of Topical Ophthalmic Products After Use (5.3) 11/2025

1 INDICATIONS AND USAGE

Brimonidine tartrate ophthalmic solution, 0.15% is an alpha adrenergic agonist indicated for the lowering of intraocular pressure (IOP) in patients with open-angle glaucoma or ocular hypertension (1).

2 DOSAGE AND ADMINISTRATION

- Instill one drop in the affected eye(s) three-times daily (2).
- If more than one topical ophthalmic product is being used, the products should be administered at least 5 minutes apart (2).

3 DOSAGE FORMS AND STRENGTHS

Ophthalmic solution containing 0.15% (1.5 mg/mL) brimonidine tartrate (3)

4 CONTRAINDICATIONS

- Neonates and infants (pediatric patients younger than 2 years old) (4.1).
- Hypersensitivity to any component of this product (4.2).

5 WARNINGS AND PRECAUTIONS

- Potentiation of vascular insufficiency (5.1)

6 ADVERSE REACTIONS

Most common adverse reactions are allergic conjunctivitis, conjunctival hyperemia, and eye pruritis (6.1).

To report SUSPECTED ADVERSE REACTIONS, contact Sandoz Inc. at 1-800-525-8747 or FDA at 1-800-FDA-1088 or www.fda.gov/medwatch.

7 DRUG INTERACTIONS

- Concomitant use with systemic beta-blockers may potentiate systemic beta-blockade (7.1).
- Use with CNS depressants may result in an additive or potentiating effect (7.2).
- Tricyclic antidepressants may potentially blunt the hypotensive effect of systemic clonidine (7.3).
- Monoamine oxidase inhibitors may result in increased hypotension (7.4).

8 USE IN SPECIFIC POPULATIONS

Use with caution in pediatric patients aged 2 years and older (8.4).

FULL PRESCRIBING INFORMATION

1 INDICATIONS AND USAGE

Brimonidine tartrate ophthalmic solution, 0.15% is indicated for the lowering of intraocular pressure in patients with open-angle glaucoma or ocular hypertension.

2 DOSAGE AND ADMINISTRATION

The recommended dosage is one drop of brimonidine tartrate ophthalmic solution, 0.15% in the affected eye(s) three-times daily, approximately 8 hours apart.

Brimonidine tartrate ophthalmic solution, 0.15% may be used concomitantly with other topical ophthalmic drug products to lower intraocular pressure. If more than one topical ophthalmic product is being used, the products should be administered at least 5 minutes apart.

3 DOSAGE FORMS AND STRENGTHS

Ophthalmic solution containing 0.15% (1.5 mg/mL) brimonidine tartrate.

4 CONTRAINDICATIONS

4.1 Neonates and Infants (Pediatric Patients Younger than 2 Years Old)

Brimonidine tartrate ophthalmic solution, 0.15% is contraindicated in neonates and infants (pediatric patients younger than 2 years old) [see Use in Specific Populations (8.4)].

4.2 Hypersensitivity Reactions

Brimonidine tartrate ophthalmic solution, 0.15% is contraindicated in patients with hypersensitivity to any component of this product [see Adverse Reactions (6.1) and (6.2)].

5 WARNINGS AND PRECAUTIONS

5.1 Potentiation of Vascular Insufficiency

Brimonidine tartrate ophthalmic solution, 0.15% may potentiate syndromes associated with vascular insufficiency. Brimonidine tartrate ophthalmic solution, 0.15% should be used with caution in patients with depression, cerebral or coronary insufficiency, Raynaud's phenomenon, orthostatic hypotension, or thromboangiitis obliterans.

5.2 Severe Cardiovascular Disease

Although brimonidine tartrate ophthalmic solution had minimal effect on the blood pressure of patients in clinical studies, caution should be exercised in treating patients with severe cardiovascular disease.

5.3 Contamination of Topical Ophthalmic Products After Use

There have been reports of bacterial keratitis associated with the use of multiple-dose containers of topical ophthalmic products. These containers had been inadvertently contaminated by patients who, in most cases, had a concurrent corneal disease or a disruption of the ocular epithelial surface.

6 ADVERSE REACTIONS

The following clinically significant adverse reactions are described elsewhere in the labeling:

- Neonates and Infants (Pediatric Patients Younger than 2 Years Old) [see Contraindications (4.1)]
- Potentiation of Vascular Insufficiency [see Warnings and Precautions (5.1)]
- Severe Cardiovascular Disease [see Warnings and Precautions (5.2)]
- Contamination of Topical Ophthalmic Products After Use [see Warnings and Precautions (5.3)]

6.1 Clinical Trials Experience

Because clinical trials are conducted under widely varying conditions, adverse reaction rates observed in the clinical trials of a drug cannot be directly compared to rates in the clinical trials of another drug and may not reflect the rates observed in practice.

Adverse reactions occurring in approximately 10 to 20% of the subjects included: allergic conjunctivitis, conjunctival hyperemia, and eye pruritis.

Adverse reactions occurring in approximately 5 to 9% of the subjects included: burning sensation, conjunctival folliculosis, hypertension, ocular allergic reaction, oral dryness, and visual disturbance.

Adverse reactions occurring in approximately 1 to 4% of subjects included: allergic reaction, arthralgia, arthritis, asthenia, blepharitis, blepharoconjunctivitis, blurred vision, bronchitis, cataract, chest pain, conjunctival edema, conjunctival hemorrhage, conjunctivitis, cough, dizziness, diabetes mellitus, dyspepsia, dyspnea, epiphora, eye discharge, eye dryness, eye irritation, eye pain, eyelid edema, eyelid erythema, fatigue, flu syndrome, follicular conjunctivitis, foreign body sensation, gastrointestinal disorder, headache, hypercholesterolemia, hypotension, infection, insomnia, joint disorder, keratitis, lid disorder, osteoporosis, pharyngitis, photophobia, rash, rhinitis, sinus infection, sinusitis, somnolence, stinging, superficial punctate keratopathy, tearing, visual field defect, vitreous detachment, vitreous disorder, vitreous floaters, and worsened visual acuity.

The following adverse reactions were reported in less than 1% of subjects: corneal erosion, nasal dryness, and taste perversion.

6.2 Postmarketing Experience

The following adverse reactions have been identified during postapproval use of brimonidine tartrate ophthalmic solution. Because these reactions are reported voluntarily from a population of uncertain size, it is not always possible to reliably estimate their frequency or establish a causal relationship to drug exposure.

- Bradycardia, iritis, miosis, skin reactions (including erythema, eyelid pruritis, rash, and vasodilation), and tachycardia.
- Apnea, bradycardia, hypotension, hypothermia, hypotonia, and somnolence have been reported in infants receiving brimonidine tartrate ophthalmic solutions.

7 DRUG INTERACTIONS

7.1 Anti-hypertensives / Cardiac Glycosides

Alpha-2 agonists, as a class, may reduce blood pressure. Caution in using drugs such as beta-blockers (ophthalmic and systemic), anti-hypertensives and/or cardiac glycosides is advised.

7.2 CNS Depressants

Although specific drug interaction studies have not been conducted with brimonidine tartrate ophthalmic solution, 0.15%, the possibility of an additive or potentiating effect with CNS depressants (alcohol, barbiturates, opiates, sedatives, or anesthetics) should be considered.

7.3 Tricyclic Antidepressants

Tricyclic antidepressants have been reported to blunt the hypotensive effect of systemic clonidine. It is not known whether the concurrent use of these agents with brimonidine tartrate ophthalmic solution, 0.15% in humans can lead to resulting interference with its IOP-lowering effect. Caution, however, is advised in patients taking tricyclic antidepressants, which can affect the metabolism and uptake of circulating amines.

7.4 Monoamine Oxidase Inhibitors

Monoamine oxidase (MAO) inhibitors may theoretically interfere with the metabolism of brimonidine and potentially result in an increased systemic side-effect such as hypotension. Caution is advised in patients taking MAO inhibitors which can affect the metabolism and uptake of circulating amines.

8 USE IN SPECIFIC POPULATIONS

8.1 Pregnancy

Risk Summary

There are no adequate and well-controlled studies with brimonidine tartrate ophthalmic solution, 0.15% in pregnant women. In the U.S. general population, the estimated background risk of major birth defects and miscarriage in clinically recognized pregnancies is 2 to 4% and 15 to 20%, respectively.

In animal studies, brimonidine crossed the placenta and entered into the fetal circulation to a limited extent (see Data). Because animal reproduction studies are not always predictive of human response, brimonidine tartrate ophthalmic solution, 0.15% should be used during pregnancy only if the potential benefit to the mother justifies the potential risk to the fetus.

Data

Human Data

Limited available data from postmarketing safety reports and published literature with topical use of brimonidine tartrate ophthalmic solution in pregnant women are insufficient to inform a drug-associated risk of pregnancy-related adverse outcomes including miscarriage, stillbirth, congenital anomaly, and events experiences by offspring while breastfeeding.

Animal Data

Embryofetal studies were conducted in pregnant rabbits administered brimonidine tartrate by daily oral gavage on gestation days 6 to 18, to target the period of organogenesis. Brimonidine caused miscarriage at 5 mg/kg/day (approximately 50-times the recommended human ophthalmic dose (RHOD) based on AUC). The no observed adverse effect level (NOAEL) for developmental toxicity in rabbits was 1 mg/kg/day (approximately 6-fold the RHOD based on AUC). No treatment-related malformations were observed in rabbits. Signs of maternal sedation and fatigue were observed at all dose levels; the lowest observed adverse effect level (LOAEL) for maternal toxicity was 5 mg/kg/day, based on the dose-response for these signs.

Embryofetal studies were conducted in pregnant rats administered brimonidine tartrate by daily oral gavage on gestation days 6 to 15, to target the period of organogenesis. The NOAEL for developmental toxicity was 2.5 mg/kg/day (approximately 750-fold the RHOD based on AUC). No treatment-related malformations were observed in rats. The LOAEL for maternal toxicity was 2.5 mg/kg/day, based on signs of sedation and fatigue. The maternal NOAEL was 1 mg/kg/day (180-fold the RHOD based on AUC).

After pregnant rats received a single oral dose of ^14C-brimonidine tartrate, brimonidine and metabolites crossed the placenta and were detectable in fetal blood and organs.

8.2 Lactation

Risk Summary

It is not known whether brimonidine tartrate is excreted in human milk. In animal studies, brimonidine has been shown to cross the blood-brain barrier and is excreted into breast milk after oral administration to lactating rats (see Data). Because of the potential for serious adverse reactions, including central nervous system depression and apnea, from brimonidine tartrate ophthalmic solution, 0.15% in nursing infants, brimonidine tartrate ophthalmic solution, 0.15% is not recommended for use during lactation.

Data

Animal Data

After a single oral dose of ^14C-labeled brimonidine tartrate to lactating rats, brimonidine and metabolites were detected in milk. After male and female rats received a single oral dose of ^14C-brimonidine tartrate, brimonidine crossed the blood:brain barrier. Radiolabel was detected in the cerebellum, cerebrum, and spinal cord.

8.4 Pediatric Use

Brimonidine tartrate ophthalmic solution, 0.15% is contraindicated in pediatric patients younger than 2 years old [see Contraindications (4.1)]. During postmarketing surveillance, apnea, bradycardia, coma, hypotension, hypothermia, hypotonia, lethargy, pallor, respiratory depression, and somnolence have been reported in infants receiving brimonidine.

In a well-controlled clinical study conducted in pediatric glaucoma patients aged 2 to 7 years old, the most commonly observed adverse events with brimonidine tartrate ophthalmic solution 0.2% dosed three-times-daily were somnolence (50% to 83% in pediatric patients aged 2 to 6 years old) and decreased alertness. In pediatric patients aged 7 years and older (>20 kg), somnolence appears to occur less frequently (25%). Approximately 16% of pediatric patients on brimonidine tartrate ophthalmic solution discontinued from the study due to somnolence.

8.5 Geriatric Use

No overall differences in safety or effectiveness have been observed between elderly and other adult patients.

10 OVERDOSAGE

Limited information exists on accidental ingestion of brimonidine in adults; the only adverse reaction reported to date has been hypotension. Symptoms of brimonidine overdose have been reported in neonates, infants, and children receiving brimonidine tartrate as part of medical treatment of congenital glaucoma or accidental oral ingestion [see Use In Specific Populations (8.4)]. Treatment of an oral overdose includes supportive and symptomatic therapy; a patent airway should be maintained.

11 DESCRIPTION

Brimonidine tartrate ophthalmic solution, 0.15% (1.5 mg brimonidine tartrate per mL equivalent to 1.0 mg brimonidine free base per mL) is a relatively selective alpha-2-adrenergic agonist for topical ophthalmic use. The chemical name of brimonidine tartrate is 5-bromo-6-(2-imidazolidinylideneamino) quinoxaline L-tartrate. It is a white to off-white,

pale yellow to yellow powder. It has a molecular weight of 442.24 as the tartrate salt, and is both soluble in water (1.5 mg/mL) and in the product vehicle (3.0 mg/mL) at pH 7.2. The structural formula is:

Formula: C11H10BrN5 • C4H6O6

CAS Number: 59803-98-4

In solution, brimonidine tartrate ophthalmic solution, 0.15% has a clear, pale yellow to greenish yellow color. It has an osmolality of 250 - 350 mOsmol/kg and a pH of 6.6 to 7.4.

Contains: Active ingredient: brimonidine tartrate 1.5 mg/mL (1.5 mg/mL), Preservative: Polyquad (polyquaternium-1) 0.001% (0.01 mg/mL), Inactives: boric acid, calcium chloride, magnesium chloride, mannitol, potassium chloride, povidone, purified water, sodium borate, sodium chloride, with hydrochloric acid and/or sodium hydroxide to adjust pH.

12 CLINICAL PHARMACOLOGY

12.1 Mechanism of Action

Brimonidine tartrate ophthalmic solution, 0.15% is an alpha-2 adrenergic receptor agonist. Fluorophotometric studies in animals and humans suggest that brimonidine tartrate has a dual mechanism of action by reducing aqueous humor production and increasing uveoscleral outflow.

12.2 Pharmacodynamics

Brimonidine tartrate ophthalmic solution, 0.15% has a peak ocular hypotensive effect occurring at two hours post-dosing.

Elevated IOP presents a major risk factor in glaucomatous field loss. The higher the level of IOP, the greater the likelihood of optic nerve damage and visual field loss. Brimonidine tartrate has the action of lowering intraocular pressure with minimal effect on cardiovascular and pulmonary parameters.

12.3 Pharmacokinetics

Absorption

In a pharmacokinetic study, 14 healthy subjects (4 males and 10 females) received a single topical ocular administration of brimonidine tartrate ophthalmic solution, 0.15%, one drop per eye. The peak plasma concentrations (Cmax) and AUC0-inf were 73 ± 19 pg/mL and 375 ± 89 pg•hr/mL, respectively. Tmax was 1.7 ± 0.7 hours after dosing. The systemic half-life was approximately 2.1 hours.

Distribution

Brimonidine was approximately 29% bound to plasma proteins in healthy subjects.

Elimination

Metabolism

In humans, brimonidine is extensively metabolized by the liver.

Excretion

Urinary excretion is the major route of elimination of brimonidine and its metabolites. Approximately 87% of an orally administered radioactive dose of brimonidine was eliminated within 120 hours, with 74% of the radioactivity recovered in the urine.

13 NONCLINICAL TOXICOLOGY

13.1 Carcinogenesis, Mutagenesis, Impairment of Fertility

Carcinogenesis

No compound-related carcinogenic effects were observed in either mice or rats following a 21-month and a 24-month study, respectively. In these studies, dietary administration of brimonidine tartrate at doses up to 2.5 mg/kg/day in mice and 1.0 mg/kg/day in rats achieved 120 and 76 times the recommended human ophthalmic dose (RHOD) based on Cmax.

Mutagenesis

Brimonidine tartrate was not mutagenic or cytogenic in a series of in vitro and in vivo studies including the Ames test, chromosomal aberration assay in Chinese hamster ovary (CHO) cells, a host-mediated assay and cytogenic studies in mice, and dominant lethal assay.

Impairment of Fertility

A reproduction and fertility study in rats with brimonidine tartrate demonstrated no adverse effect on male or female fertility at oral doses up to 1 mg/kg (approximately 180 times the recommended human ophthalmic dose (RHOD) based on estimated AUC).

14 CLINICAL STUDIES

A clinical study was conducted to evaluate the safety and efficacy of brimonidine tartrate ophthalmic solution, 0.15% compared to Alphagan® P** administered three times daily in patients with open-angle glaucoma or ocular hypertension. The results indicated that brimonidine tartrate ophthalmic solution, 0.15% is equivalent in IOP-lowering effect to Alphagan® P (brimonidine tartrate ophthalmic solution), 0.15%, and effectively lowers IOP in patients with open-angle glaucoma or ocular hypertension by 2 - 6 mmHg.

16 HOW SUPPLIED/STORAGE AND HANDLING

Brimonidine tartrate ophthalmic solution, 0.15% is supplied sterile in opaque white LDPE plastic bottles and natural tips with purple polypropylene caps as follows:

5 mL in 8 mL bottle NDC 61314-144-05

10 mL in 10 mL bottle NDC 61314-144-10

15 mL in 15 mL bottle NDC 61314-144-15

Storage: Store at 15°C to 25° C (59°F to 77°F). After opening, Brimonidine tartrate ophthalmic solution, 0.15% can be used until the expiration date on the bottle.

17 PATIENT COUNSELING INFORMATION

Handling the Container

Instruct patients that ocular solutions, if handled improperly or if the tip of the dispensing container contacts the eye or surrounding structures, can become contaminated by common bacteria known to cause ocular infections. Serious damage to the eye and subsequent loss of vision may result from using contaminated solutions [see Warnings and Precautions (5.3)]. Always replace the cap after using. If solution changes color or becomes cloudy, do not use. Do not use the product after the expiration date marked on the bottle.

When to Seek Physician Advice

Advise patients that if they have ocular surgery or develop an intercurrent ocular condition (e.g., trauma or infection), they should immediately seek their physician's advice concerning the continued use of the present multidose container.

Use with Other Ophthalmic Drugs

Advise patients that if more than one topical ophthalmic drug is being used, the drugs should be administered at least five minutes apart.

Potential for Decreased Mental Alertness

As with other drugs in this class, brimonidine tartrate ophthalmic solution, 0.15% may cause fatigue and/or drowsiness in some patients. Patients who engage in hazardous activities should be cautioned of the potential for a decrease in mental alertness.

Rx Only

**ALPHAGAN P is a registered trademark of Allergan, Inc.

Manufactured by

Alcon Laboratories, Inc.

Fort Worth, Texas 76134 for

Sandoz Inc.

Princeton, NJ 08540

300069925-1125

PRINCIPLE DISPLAY PANEL

NDC 61314-144-05

Brimonidine

Tartrate

Ophthalmic

Solution

0.15%

For Topical Eye Use Only

Rx Only

STERILE

5 mL

SANDOZ